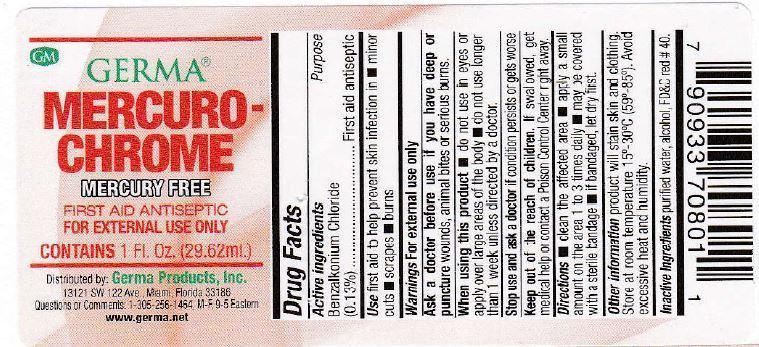 DRUG LABEL: Mercurochrome
NDC: 10095-004 | Form: CREAM
Manufacturer: World Perfumes, Inc
Category: otc | Type: HUMAN OTC DRUG LABEL
Date: 20150508

ACTIVE INGREDIENTS: BENZALKONIUM CHLORIDE 0.13 g/100 g
INACTIVE INGREDIENTS: WATER; ALCOHOL; FD&C RED NO. 40

Active Ingredients Purpose

Benzalkonium Chloride (0.13%) ................... First aid antiseptic

Use

first aid to help prevent skin infection in

- minor cuts
- scrapes
- burns

Keep out of reach of children. If swallowed, get medical help or contact a Poison Control Center right away.

INDICATIONS AND USAGE

Mercurochrome

Mercury Free

First Aid Antiseptic

For External Use Only

Directions

- clean the affected area
- apply a small amount on the area 1 to 3 times daily
- may be covered with a sterile bandage
- if bandaged, let dry first

Warnings For external use only

Ask a doctor before use if you have deep or puncture wounds, animal bites or serious burns

When using this product

- do not use in eyes or apply over large areas of the body
- do not use longer than 1 week unless directed by a doctor

Stop use and ask a doctor if condition persists or gets worse

INACTIVE INGREDIENT

Inactive Ingredients purified water, alcohol, FD&C red # 40.